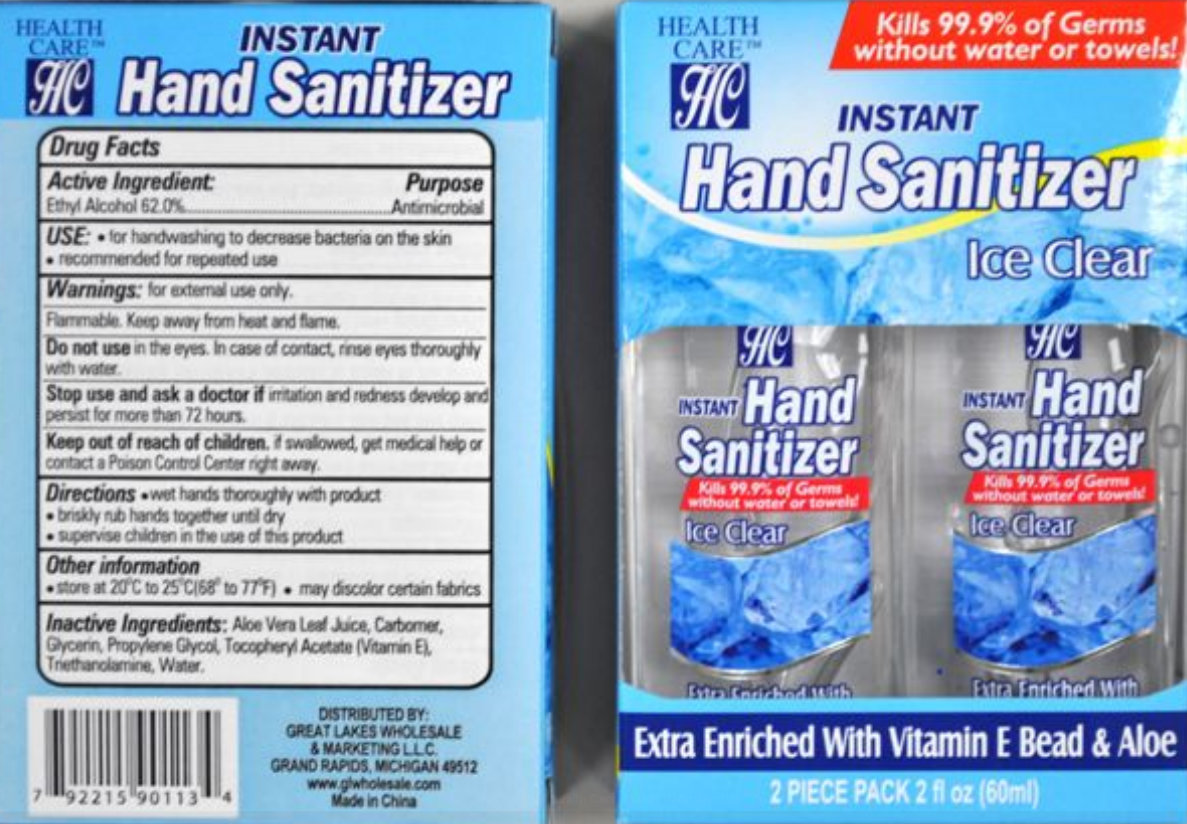 DRUG LABEL: Health Care Instant Hand Sanitizer Ice Clear
NDC: 64092-113 | Form: LIQUID
Manufacturer: GREAT LAKES WHOLESALE, MARKETING, & SALES, INC.
Category: otc | Type: HUMAN OTC DRUG LABEL
Date: 20120328

ACTIVE INGREDIENTS: ALCOHOL 62 mL/100 mL
INACTIVE INGREDIENTS: ALOE VERA LEAF; GLYCERIN; PROPYLENE GLYCOL; ALPHA-TOCOPHEROL ACETATE; TROLAMINE; WATER

Health Care Instant Hand Sanitizer Ice Clear

Active Ingredient:

Ethyl Alchohol 62.0%

Purpose

Antimicrobial

Use:

- for handwashing to decrease bacteria on the skin
- recommended for repeated use

Warnings:

for external use only.

Flammable. Keep away from heat and flame.

Do not use in the eyes. In case of contact, rinse eyes thoroughly with water.

Stop use and ask a doctor if irritation and redness develop and persist for more than 72 hours.

Keep out of reach of children. If swallowed, get medical help or contact a Poison Control Center right away.

Directions

- wet hands thoroughly with product
- briskly rub hands together until dry
- supervise children in the use of this product

Other Information

- store at 20 degrees to 25 degrees C (68 degrees to 77 degrees F)
- may discolor certain fabrics

Inactive Ingredients:

Aloe Vera Leaf Juice, Carbomer, Glycerin, Propylene Glycol, Tocopheryl Acetate (Vitamin E), Triethanolamine, Water.